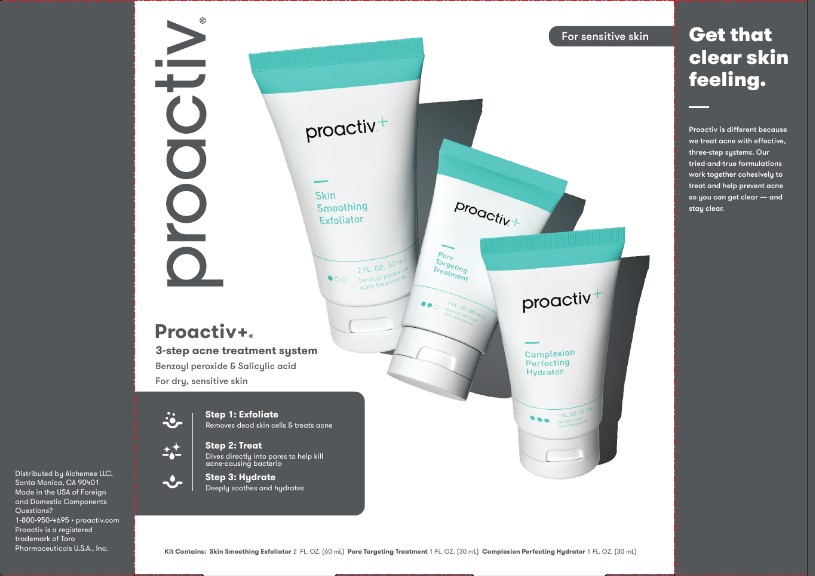 DRUG LABEL: Proactiv Plus Kit
NDC: 11410-218 | Form: KIT | Route: TOPICAL
Manufacturer: Alchemee, LLC
Category: otc | Type: HUMAN OTC DRUG LABEL
Date: 20260107

ACTIVE INGREDIENTS: BENZOYL PEROXIDE 2.5 mg/100 mL; BENZOYL PEROXIDE 2.5 g/100 mL; SALICYLIC ACID 0.5 g/100 mL
INACTIVE INGREDIENTS: SODIUM COCOYL ISETHIONATE; ETHYLHEXYLGLYCERIN; GLYCOLIC ACID; COCONUT ACID; BUTYLENE GLYCOL; PARAFFIN; GLYCERIN; WATER; PHENOXYETHANOL; SODIUM HYDROXIDE; DIMETHICONE; LINOLEIC ACID; LAURYL/MYRISTYL BENZOATE; SODIUM ISETHIONATE; TOCOPHEROL; LINOLENIC ACID; CARBOMER COPOLYMER TYPE A (ALLYL PENTAERYTHRITOL CROSSLINKED); ALMOND OIL; PHENOXYETHANOL; POLYSORBATE 60; POLYSORBATE 80; SORBITAN MONOSTEARATE; DIETHYLENE GLYCOL MONOETHYL ETHER; ETHYLHEXYLGLYCERIN; EDETATE DISODIUM ANHYDROUS; WATER; CAPRYLYL GLYCOL; POTASSIUM HYDROXIDE; GLYCERIN; CARBOMER HOMOPOLYMER, UNSPECIFIED TYPE; KOJIC ACID; HYDROGENATED POLYDECENE TYPE I; SQUALANE; WATER; SCUTELLARIA BAICALENSIS ROOT; PHENOXYETHANOL; DIMETHICONE; LEVOMENOL; SODIUM HYDROXIDE; SOPHORA FLAVESCENS ROOT; PPG-2 MYRISTYL ETHER PROPIONATE; ARCTOSTAPHYLOS UVA-URSI LEAF; ZINC GLUCONATE; HYALURONATE SODIUM; MORUS ALBA ROOT; ALUMINUM STARCH OCTENYLSUCCINATE; POLYOXYL 20 CETOSTEARYL ETHER; GLYCYRRHIZA GLABRA; GLYCERIN; CAPRYLYL GLYCOL; CETOSTEARYL ALCOHOL; .ALPHA.-GLUCAN OLIGOSACCHARIDE; ALLANTOIN; ETHYLHEXYLGLYCERIN; C12-15 ALKYL LACTATE; POLYSORBATE 60; HEXYLENE GLYCOL; ETHYLHEXYL PALMITATE; EDETATE DISODIUM; ADRABETADEX; BUTYLENE GLYCOL; SODIUM POLYACRYLATE (8000 MW); MEDIUM-CHAIN TRIGLYCERIDES; POLYQUATERNIUM-11 (1000000 MW)

Proactiv Plus Kit

Skin Smoothing Exfoliator - Drug Facts

Drug Facts

Pore Targeting Treatment - Drug Facts

Drug Facts

Complexion Perfecting Hydrator - Drug facts

Drug Facts

Skin Smoothing Exfoliator - Active ingredient

Benzoyl peroxide 2.5%

Pore Targeting Treatment - Active Ingredient

Benzoyl peroxide 2.5%

Complexion Perfecting Hydrator - Active Ingredients

Salicylic Acid 0.5%

Skin Smoothing Exfoliator - Purpose

Acne treatment

Pore Targeting Treatment - Purpose

Acne treatment

Complexion Perfecting Hydrator - Purpose

Acne Treatment

Complexion Perfecting Hydrator - Use

for the management of acne

Skin Smoothing Exfoliator - Use

for the management of acne

Pore Targeting Treatment - Use

for the management of acne

Skin Smoothing Exfoliator - Warnings

For external use only

Pore Targeting Treatment - Warnings

For external use only

Complexion Perfecting Hydrator - Warnings

For external use only

Skin Smoothing Exfoliator - When using this product

skin irritation and dryness is more likely to occur if you use another topical acne medication at the same time. If irritation occurs, only use one topical acne medication at a time.
avoid unnecessary sun exposure and use a sunscreen.
avoid contact with eyes, lips and mouth.
avoid contact with hair and dyed fabrics, which may be bleached by this product.

skin irritation may occur, characterized by redness, burning, itching, peeling or possibly swelling. Irritation may be reduced by using the product less frequently or in a lower concentration.

Pore Targeting Treatment - When using this product

skin irritation and dryness is more likely to occur if you use another topical acne medication at the same time. If irritation occurs, only use one topical acne medication at a time.
avoid unnecessary sun exposure and use a sunscreen.
avoid contact with eyes, lips and mouth.
avoid contact with hair and dyed fabrics, which may be bleached by this product.

skin irritation may occur, characterized by redness, burning, itching, peeling or possibly swelling. Irritation may be reduced by using the product less frequently or in a lower concentration.

Complexion Perfecting Hydrator - when using this product

skin irritation and dryness is more likely to occur if you use another topical acne medication at the same time. If irritation occurs, only use one topical acne medication at a time.

avoid contact with eyes. If contact occurs rinse eyes thoroughly with water.

Skin Smoothing Exfoliator - Do not use if you

- have very sensitive skin.
- are sensitive to benzoyl peroxide

Pore Targeting Treatment - Do not use if you

have very sensitive skin.

are sensitive to benzoyl peroxide.

Skin Smoothing Exfoliator - Stop use and ask a doctor if

If irritation becomes Severe

Pore Targeting Treatment - Stop use and ask a doctor if

If irritation becomes severe.

Complexion Perfecting Hydrator - Stop use and ask a doctor if

If irritation becomes Severe

Skin Smoothing Exfoliator - Keep out of reach of children

If swallowed, call a Poison Control Center or get medical help right away.

Repairing Treatment - Keep out of reach of children

If swallowed, call a Poison Control Center or get medical help right away.

Pore Targeting Treatment - Keep out of reach of children

If swallowed, call a Poison Control Center or get medical help right away.

Complexion Perfecting Hydrator - Keep out of reach of children

If swallowed, call a Poison Control Center or get medical help right away.

Skin Smoothing Exfoliator - Directions

- Sensitivity Test for a New User . Apply product sparingly to one or two small affected areas during the first 3 days. If no discomfort occurs, follow the directions stated below.
- cover the entire affected area with a thin layer and rinse thoroughlyone to three times daily.
- because excessive drying of the skin may occur, start with one application daily, then gradually increase to two or three times daily if needed or as directed by a doctor.
- if bothersome dryness or peeling occurs, reduce application to once a day or every other day.
- if going outside, apply sunscreen after using this product. If irritation or sensitivity develops, stop use of both products and ask a doctor.

Pore Targeting Treatment - Directions

Sensitivity Test for a New User. Apply product sparingly to one or two small affected areas during the first 3 days. If no discomfort occurs, follow the directions stated below.
clean the skin thoroughly before applying this product.
cover the entire affected area with a thin layer one to three times daily.
because excessive drying of the skin may occur, start with one application daily, then gradually increase to two or three times daily if needed or as directed by a doctor.
if bothersome dryness or peeling occurs, reduce application to once a day or every other day.

if going outside, apply sunscreen after using this product. If irritation or sensitivity develops, stop use of both products and ask a doctor.

Complexion Perfecting Hydrator - Directions

Sensitivity Test for a New User. Apply product sparingly to one or two small affected areas during the first 3 days. If no discomfort occurs, follow the directions stated below.

clean the skin thoroughly before applying this product.

cover the entire affected area with a thin layer one to three times daily.
because excessive drying of the skin may occur, start with one application daily, then gradually increase to two or three times daily if needed or as directed by a doctor.

if bothersome dryness or peeling occurs, reduce application to once a day or every other day.

Skin Smoothing Exfoliator - Inactive ingredients

Water, Sodium Cocoyl Isethionate, Glycerin, Paraffin, Lauryl/Myristyl Benzoate, Coconut Acid, Butylene Glycol, Acrylates/C10-30 Alkyl Acrylate Crosspolymer, Phenoxyethanol, Sodium Isethionate, Sodium Hydroxide, Fragrance, Dimethicone, Linoleic Acid, Ethylhexylglycerin, Glycolic Acid, Linolenic Acid.

Pore Targeting Treatment - Inactive Ingredient

water, ethoxydiglycol, glycerin, phenoxyethanol, sorbitan stearate, polysorbate 60, carbomer, caprylyl glycol, prunus amygdalus dulcis (sweet almond) oil, potassium hydroxide, polysorbate 80, ethylhexylglycerin, fragrance, disodium EDTA

Complexion Perfecting Hydrator - Inactive Ingredients

water, butylene glycol, cetearyl alcohol, dimethicone, sodium polyacrylate, glycerin, ceteareth-20, ethylhexyl palmitate, polysorbate 60, hydrogenated polydecene, aluminum starch octenylsuccinate, PPG-2 myristyl ether propionate, phenoxyethanol, alpha-glucan oligosaccharide, squalane, caprylic/capric triglyceride, caprylyl glycol, zinc gluconate, C12-15 alkyl lactate, morus alba root extract, hexylene glycol, ethylhexylglycerin, bisabolol, safflower oil/palm oil aminopropanediol esters, allantoin, PPG-5-laureth-5, sodium hydroxide, kojic acid, hydroxypropyl cyclodextrin, sophora angustifolia root extract, disodium edta, fragrance, polyquaternium-11, glycyrrhiza glabra (licorice) root extract, arctostaphylos uva ursi leaf extract, scutellaria baicalensis root extract, sodium hyaluronate.

Questions or comments?

1-800-950-4695

Distributed by Alchemee LLC
Santa Monica, CA 90401
Made in the USA of Foreign
and Domestic Components
Questions? 1-800-950-4695 • proactiv.com
Proactiv is a registered trademark
of Taro Pharmaceuticals U.S.A., Inc.

PRINCIPAL DISPLAY PANEL - Proactiv Plus Kit

proactiv®

Proactiv+

3-Step Acne Treatment System

Benzoyl Peroxide & Salicylic Acid

For dry, sensitive skin

Step 1: Exfoliate

Removes dead skin cells & treats acne

Step 2: Treat

Dives directly into pores to help kill acne-causing bacteria

Step 3: Hydrate

Deeply soothes and Hydrates

Kits Contains: Skin Smoothing Exfoliator 2 FL. OZ. (60 mL) Pore Targeting Treatment 1 FL. OZ. (30 mL) Complexion Perfecting Hydrator 1 FL. OZ. (30mL)